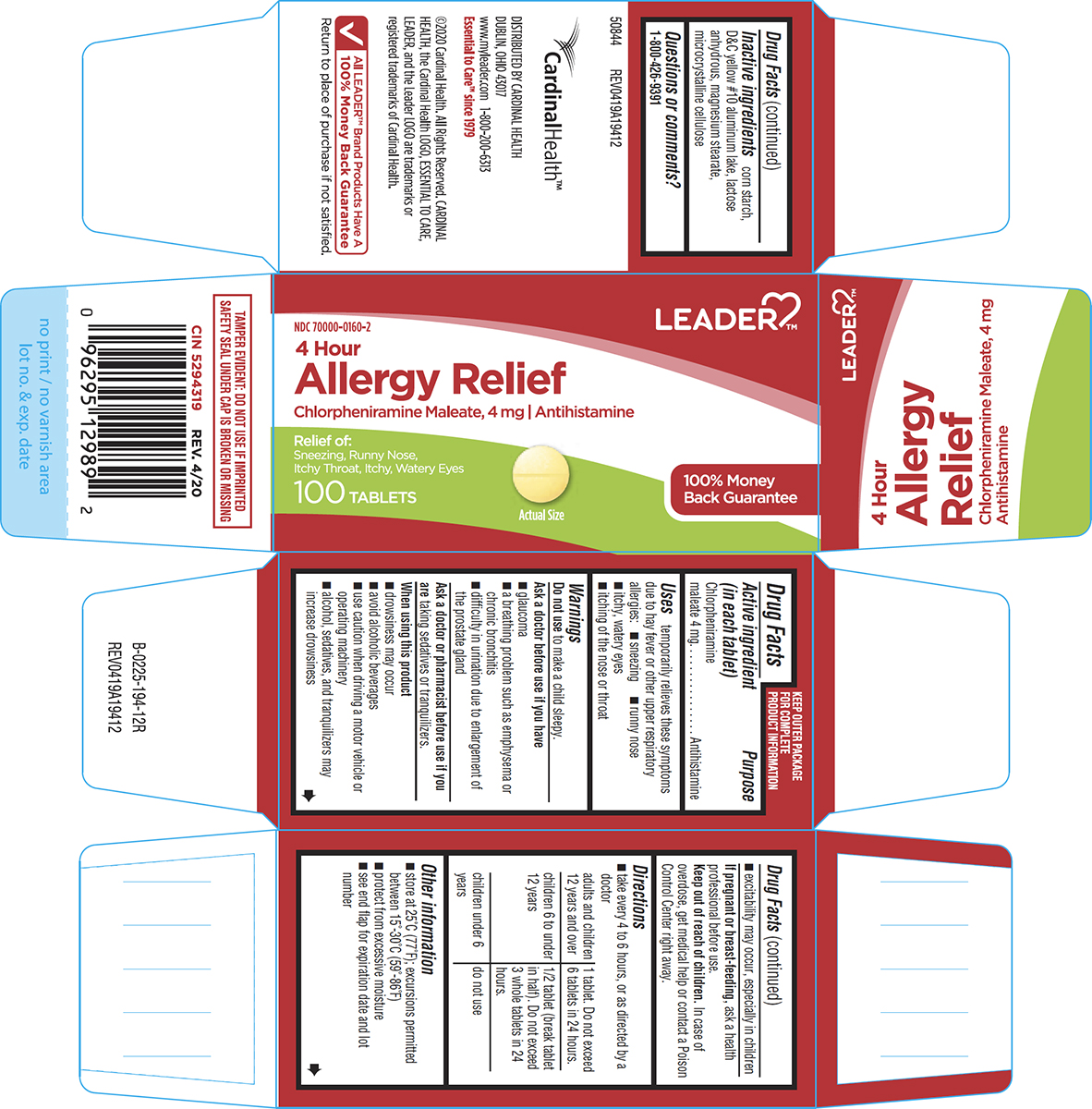 DRUG LABEL: Allergy Relief
NDC: 70000-0160 | Form: TABLET
Manufacturer: Cardinal Health 110, LLC. DBA Leader
Category: otc | Type: HUMAN OTC DRUG LABEL
Date: 20250719

ACTIVE INGREDIENTS: CHLORPHENIRAMINE MALEATE 4 mg/1 1
INACTIVE INGREDIENTS: STARCH, CORN; D&C YELLOW NO. 10 ALUMINUM LAKE; ANHYDROUS LACTOSE; MAGNESIUM STEARATE; MICROCRYSTALLINE CELLULOSE

Leader 44-194

Active ingredient (in each tablet)

Chlorpheniramine maleate 4 mg

Purpose

Antihistamine

Uses

temporarily relieves these symptoms due to hay fever or other upper respiratory allergies:

- sneezing
- runny nose
- itchy, watery eyes
- itching of the nose or throat

Warnings

Do not use

to make a child sleepy.

Ask a doctor before use if you have

- glaucoma
- a breathing problem such as emphysema or chronic bronchitis
- difficulty in urination due to enlargement of the prostate gland

Ask a doctor or pharmacist before use if you are

taking sedatives or tranquilizers.

When using this product

- drowsiness may occur
- avoid alcoholic beverages
- use caution when driving a motor vehicle or operating machinery
- alcohol, sedatives, and tranquilizers may increase drowsiness
- excitability may occur, especially in children

If pregnant or breast-feeding,

ask a health professional before use.

Keep out of reach of children.

In case of overdose, get medical help or contact a Poison Control Center right away.

Directions

- take every 4 to 6 hours, or as directed by a doctor

adults and children 12 years and over | 1 tablet. Do not exceed 6 tablets in 24 hours.
children 6 to under 12 years | 1/2 tablet (break tablet in half). Do not exceed 3 whole tablets in 24 hours.
children under 6 years | do not use

Other information

- store at 25°C (77°F); excursions permitted between 15°-30°C (59°-86°F)
- protect from excessive moisture
- see end flap for expiration date and lot number

Inactive ingredients

corn starch, D&C yellow #10 aluminum lake, lactose anhydrous, magnesium stearate, microcrystalline cellulose

Questions or comments?

1-800-426-9391

Principal display panel

LEADER™

NDC 70000-0160-2

4 Hour
Allergy Relief

Chlorpheniramine Maleate, 4 mg | Antihistamine

Relief of:
Sneezing, Runny Nose,
Itchy Throat, Itchy, Watery Eyes

100 TABLETS

Actual Size

100% Money
Back Guarantee

TAMPER EVIDENT: DO NOT USE IF IMPRINTED
SAFETY SEAL UNDER CAP IS BROKEN OR MISSING

CIN 5294319 REV. 4/20

50844 REV0419A19412

CardinalHealth™

DISTRIBUTED BY CARDINAL HEALTH
DUBLIN, OHIO 43017
www.myleader.com 1-800-200-6313
Essential to Care™ since 1979

©2020 Cardinal Health. All Rights Reserved. CARDINAL
HEALTH, the Cardinal Health LOGO, ESSENTIAL TO CARE,
LEADER, and the Leader LOGO are trademarks or
registered trademarks of Cardinal Health.

All LEADER™ Brand Products Have A
100% Money Back Guarantee
Return to place of purchase if not satisfied.

Leader 44-194